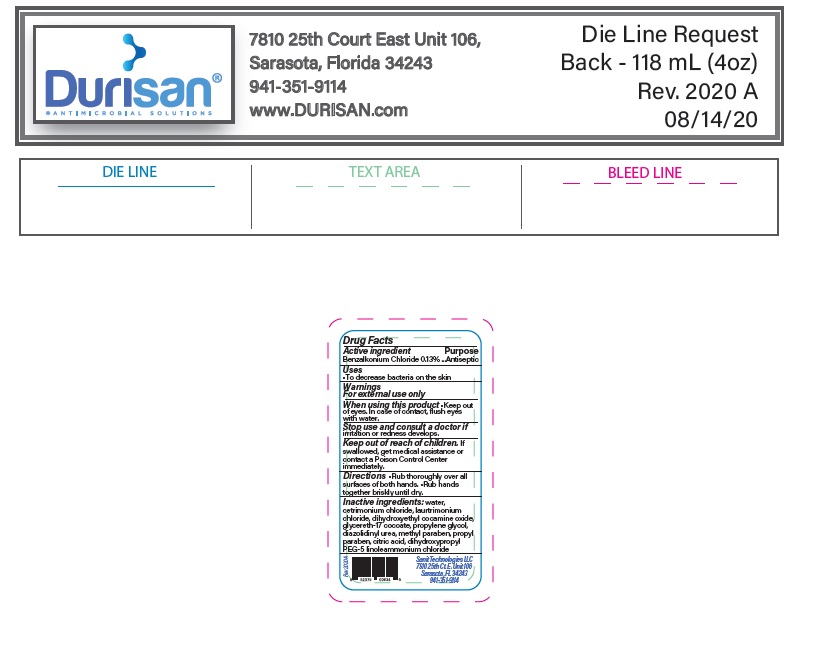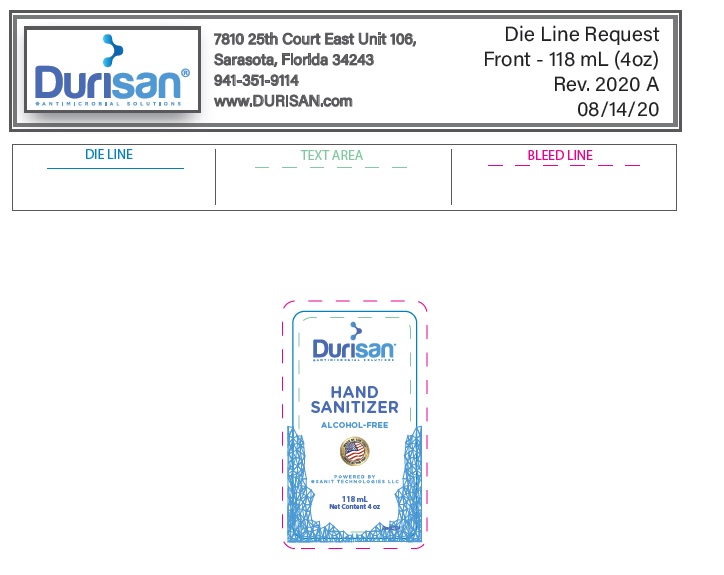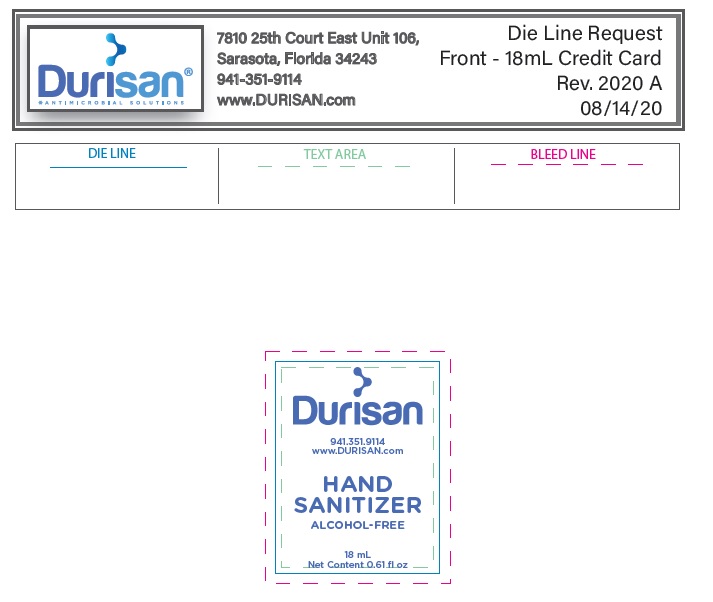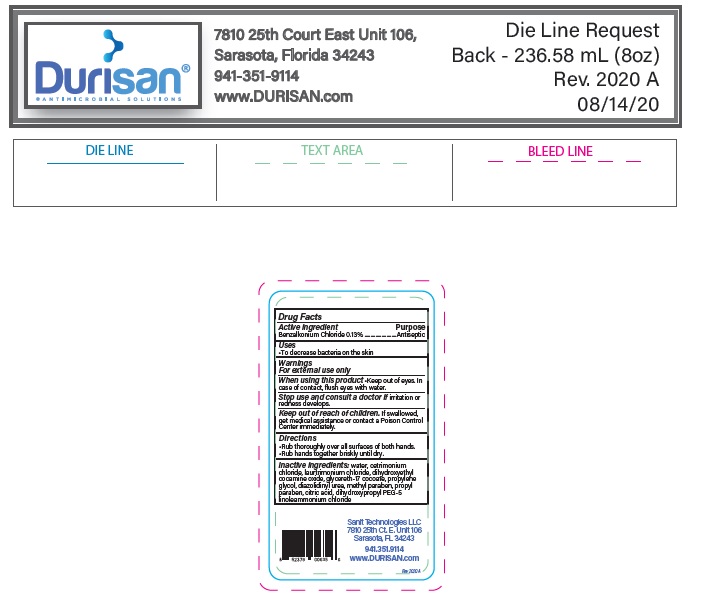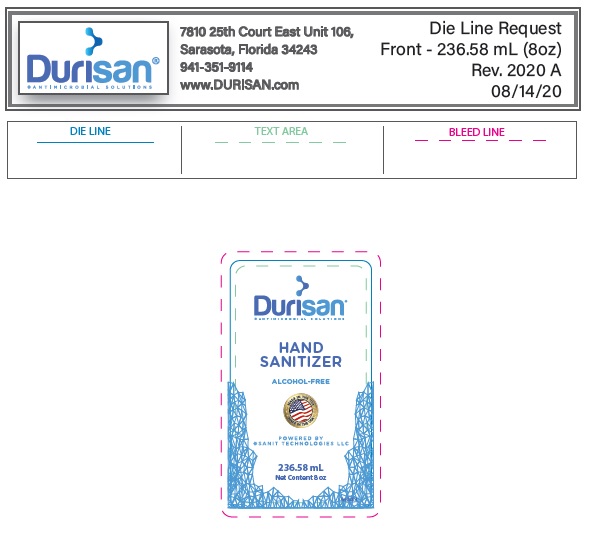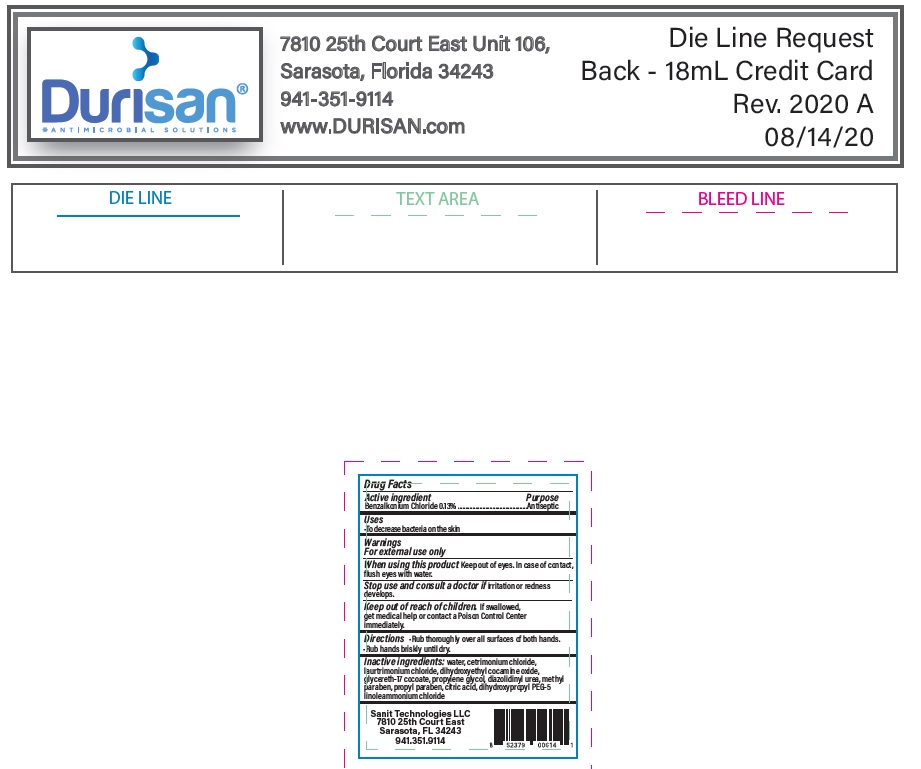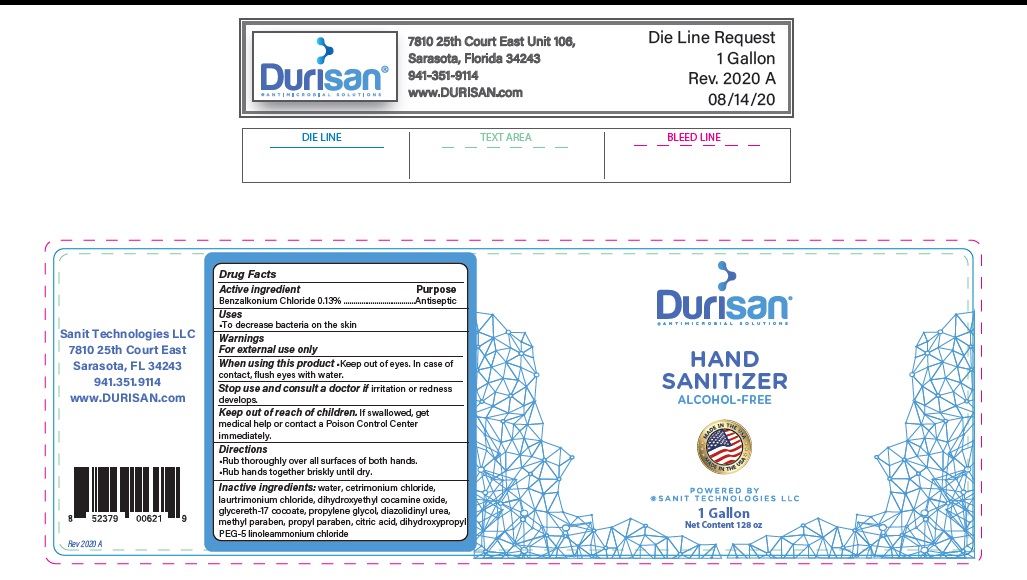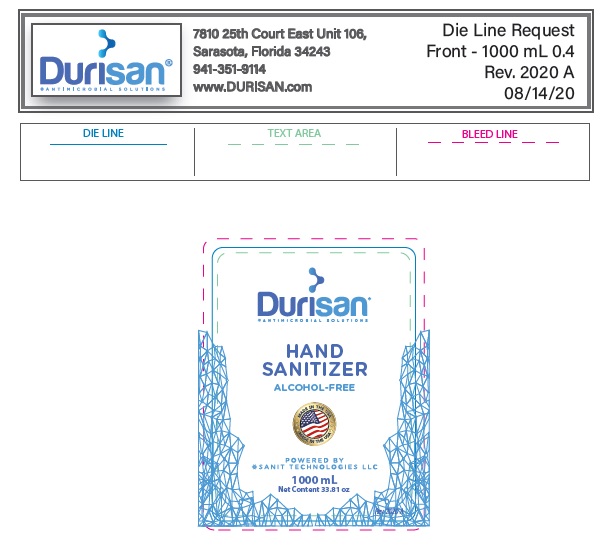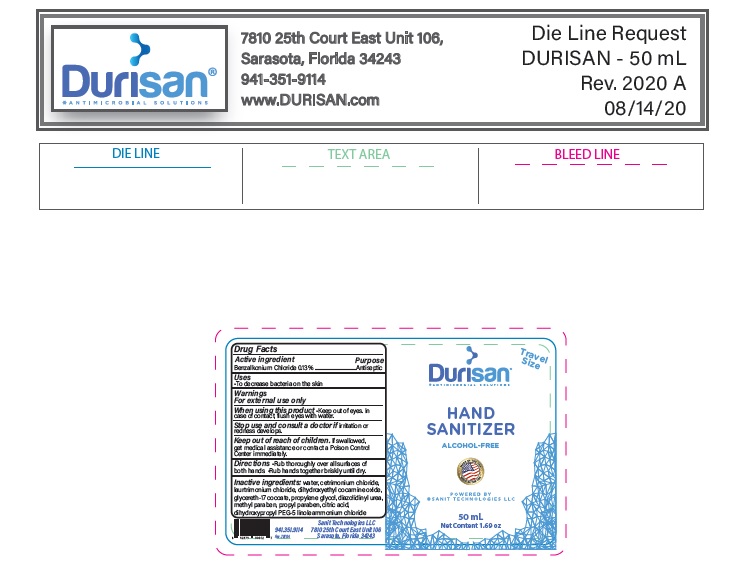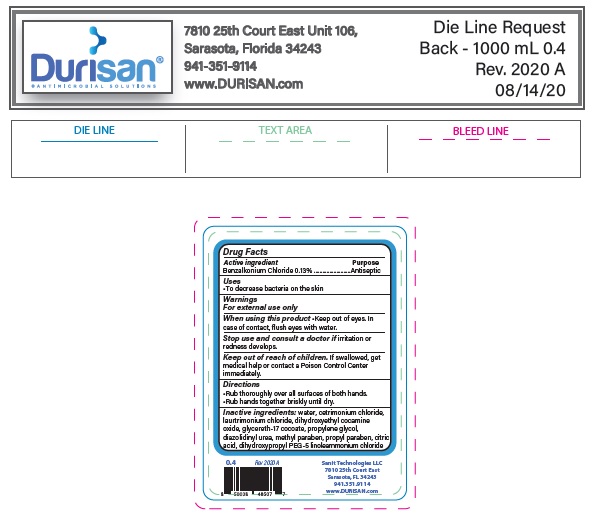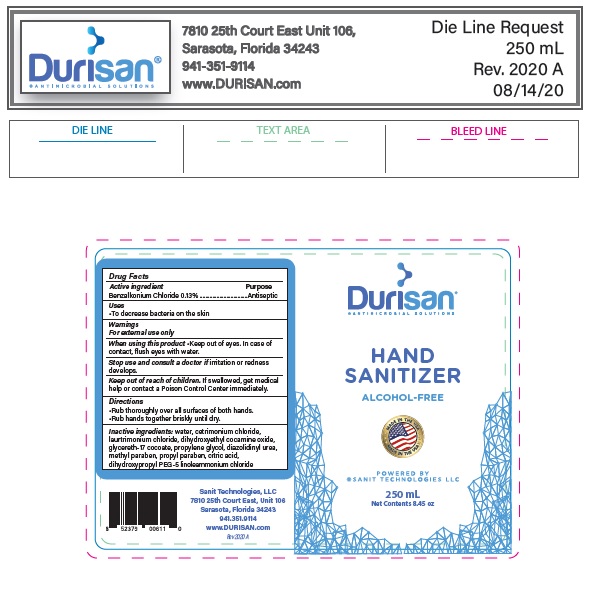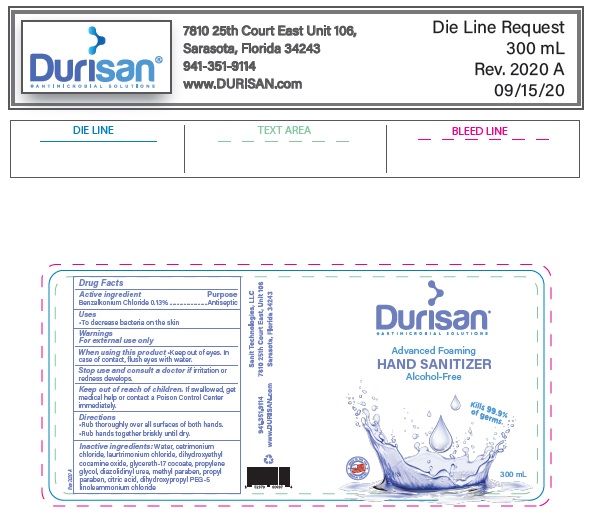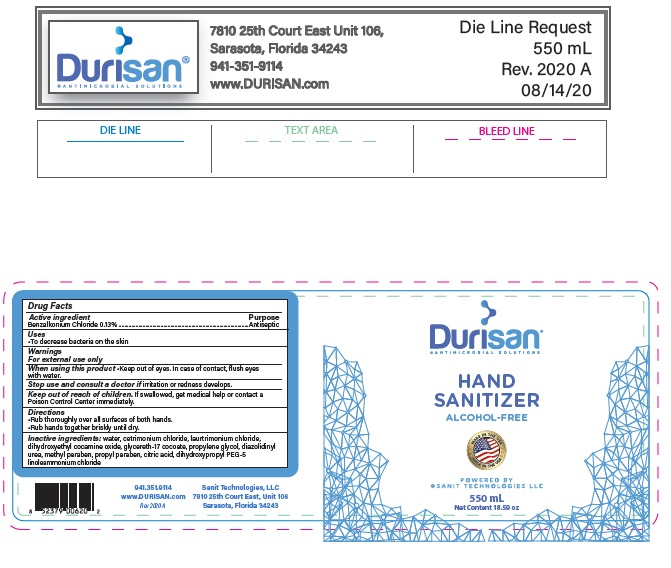 DRUG LABEL: Hand Sanitizer
NDC: 71120-112 | Form: LIQUID
Manufacturer: Sanit Technologies LLC
Category: otc | Type: HUMAN OTC DRUG LABEL
Date: 20201111

ACTIVE INGREDIENTS: BENZALKONIUM CHLORIDE 1.3 mg/1 mL
INACTIVE INGREDIENTS: WATER; CETRIMONIUM CHLORIDE; LAURTRIMONIUM CHLORIDE; DIHYDROXYETHYL COCAMINE OXIDE; GLYCERETH-17 COCOATE; PROPYLENE GLYCOL; DIAZOLIDINYL UREA; METHYLPARABEN; PROPYLPARABEN; CITRIC ACID MONOHYDRATE; DIHYDROXYPROPYL PEG-5 LINOLEAMMONIUM CHLORIDE

18ml Hand Sanitizer Credit Card Sprayer

Active Ingredient

Benzalkonium Chloride 0.13%

Purpose

Antiseptic

Warnings

- For external use only.
- Keep out of eyes. In case of contact, flush eyes water.
- Stop use and consult a doctor if irritation or redness develops.

Uses

• To decrease bacteria on the skin.

Directions

•Rub thoroughly over all surfaces of both hands.
•Rub hands together briskly until dry.

Keep out of reach of children.

- If swallowed, get medical help or contact a Poison Control Center immediately.

Inactive ingredients:

water, Cetrimonium chloride, laurtrimonium chloride, dihydroxyethyl cocamine oxide, glycereth-17 cocoate, propylene glycol, diazolidinyl urea, methyl paraben, propylparaben, citric acid, dihydroxypropyl, PEG-5 linoleammonium.